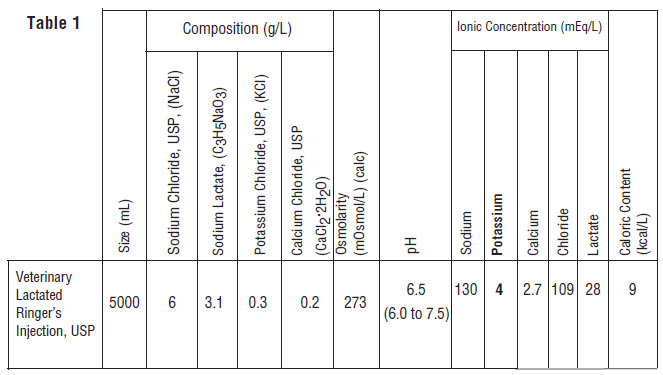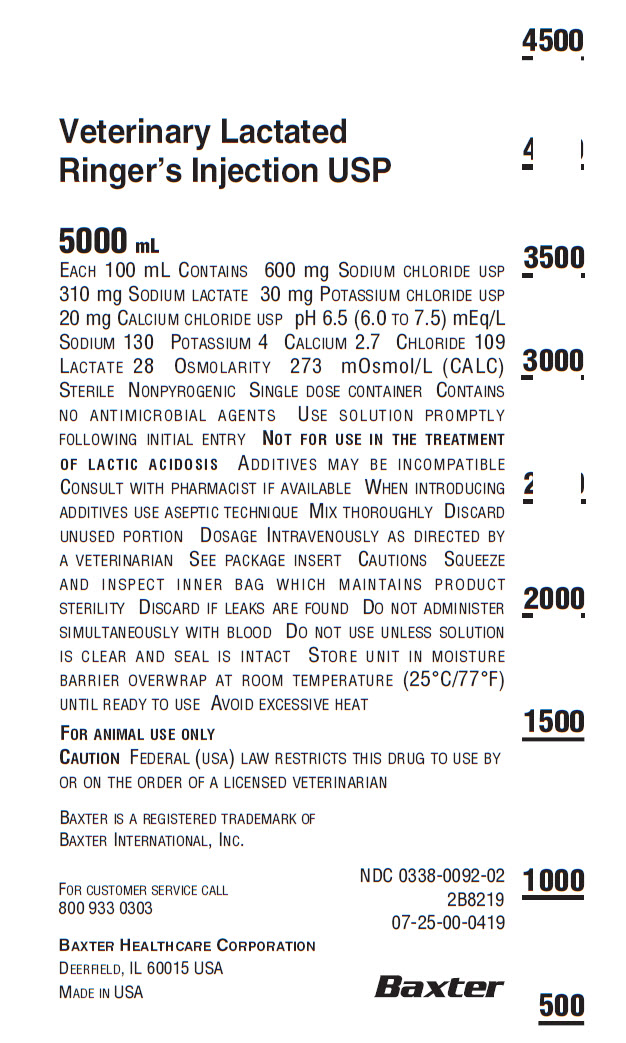 DRUG LABEL: Veterinary Lactated Ringers
NDC: 0338-0092 | Form: INJECTION, SOLUTION
Manufacturer: Baxter Healthcare Corporation
Category: animal | Type: PRESCRIPTION ANIMAL DRUG LABEL
Date: 20190101

ACTIVE INGREDIENTS: SODIUM CHLORIDE 600 mg/100 mL; SODIUM LACTATE 310 mg/100 mL; POTASSIUM CHLORIDE 30 mg/100 mL; CALCIUM CHLORIDE 20 mg/100 mL
INACTIVE INGREDIENTS: WATER

Veterinary Lactated Ringer’s Injection, USP
For Animal Use Only

DESCRIPTION

Lactated Ringer’s Injection, USP is a sterile, nonpyrogenic solution for fluid and electrolyte replenishment in single dose containers for
intravenous administration. It contains no antimicrobial agents. Discard unused portion. Composition, osmolarity, pH, ionic concentration and caloric content are shown in Table 1.

The plastic container is fabricated from a specially formulated polyvinyl chloride. The amount of water that can permeate from inside the container into the overwrap is insufficient to affect the solution significantly. Solutions in contact with the plastic container can leach out certain of its chemical components in very small amounts within the expiration period, e.g., di-2-ethylhexyl phthalate (DEHP), up to 5 parts per million. However, the safety of the plastic has been confirmed in tests in animals according to USP biological tests for plastic containers as well as by tissue culture toxicity studies.

CLINICAL PHARMACOLOGY

Lactated Ringer’s Injection, USP has value as a source of water and
electrolytes. It is capable of inducing diuresis depending on the clinical condition of the patient.

Lactated Ringer’s Injection, USP produces a metabolic alkalinizing effect. Lactate ions are metabolized ultimately to carbon dioxide and water, which requires the consumption of hydrogen cations.

INDICATIONS AND USAGE

Lactated Ringer’s Injection, USP is indicated as a source of water and electrolytes or as an alkalinizing agent.

CONTRAINDICATIONS

None known

WARNINGS

Lactated Ringer’s Injection, USP should be used with great care, if at all, in patients with congestive heart failure, severe renal insufficiency, and in clinical states in which there exists edema with sodium retention.

Lactated Ringer’s Injection, USP should be used with great care, if at all, in patients with hyperkalemia, severe renal failure, and in conditions in which potassium retention is present.

Lactated Ringer’s Injection, USP should be used with great care in patients with metabolic or respiratory alkalosis. The administration of lactate ions should be done with great care in those conditions in which there is an increased level or an impaired utilization of these ions, such as severe hepatic insufficiency.

Lactated Ringer’s Injection, USP should not be administered simultaneously with blood through the same administration set because of the likelihood of coagulation.

The intravenous administration of Lactated Ringer’s Injection, USP can cause fluid and/or solute overloading resulting in dilution of serum
electrolyte concentrations, overhydration, congested states, or pulmonary edema. The risk of dilutional states is inversely proportional to the electrolyte concentrations of the injections. The risk of solute overload causing congested states with peripheral and pulmonary edema is directly proportional to the electrolyte concentrations of the injections.

In patients with diminished renal function, administration of Lactated Ringer’s Injection, USP may result in sodium or potassium retention.

Lactated Ringer’s Injection, USP is not for use in the treatment of lactic acidosis.

ADVERSE REACTIONS

Reactions which may occur because of the solution or the technique of administration include febrile response, infection at the site of injection, venous thrombosis or phlebitis extending from the site of injection, extravasation, and hypervolemia. If an adverse reaction does occur, discontinue the infusion, evaluate the patient, institute appropriate therapeutic countermeasures, and save the remainder of the fluid for examination if deemed necessary.

PRECAUTIONS

Clinical evaluation and periodic laboratory determinations are necessary to monitor changes in fluid balance, electrolyte concentrations, and acid base balance during prolonged parenteral therapy or whenever the condition of the patient warrants such evaluation.

Lactated Ringer’s Injection, USP must be used with caution. Excess administration may result in metabolic alkalosis.

Caution must be exercised in the administration of Lactated Ringer’s Injection, USP to patients receiving corticosteroids or corticotropin.

Do not administer unless solution is clear and seal is intact.

Reactions which may occur because of the solution or the technique of administration include febrile response, infection at the site of injection, venous thrombosis or phlebitis extending from the site of injection, extravasation, and hypervolemia.

If an adverse reaction does occur, discontinue the infusion, evaluate the patient, institute appropriate therapeutic countermeasures, and save the remainder of the fluid for examination if deemed necessary.

DOSAGE AND ADMINISTRATION

As directed by a veterinarian. Dosage is dependent upon the age, weight and clinical condition of the patient as well as laboratory determinations.

Parenteral drug products should be inspected visually for particulate matter and discoloration prior to administration whenever solution and container permit.

All injections in plastic containers are intended for intravenous administration using sterile equipment.

Additives may be incompatible. Complete information is not available. Those additives known to be incompatible should not be used. Consult with pharmacist, if available. If, in the informed judgment of the veterinarian, it is deemed advisable to introduce additives, use aseptic technique. Mix thoroughly when additives have been introduced. Do not store solutions containing additives.

OVERDOSAGE

In an event of overhydration or solute overload, re-evaluate the patient and institute appropriate corrective measures. See Warnings, Precautions and Adverse Events.

HOW SUPPLIED

Lactated Ringer’s Injection, USP in plastic container is available as follows:
Size (mL) Code NDC
5000 2B8219 NDC 0338-0092-02
Exposure of pharmaceutical products to heat should be minimized. Avoid excessive heat. It is recommended the product be stored at room temperature (25°C); brief exposure up to 40°C does not adversely affect the product.

Directions for use of plastic container

To Open

Tear overwrap down side at slit and remove solution container. Visually inspect the container. If the outlet port protector is damaged, detached, or not present, discard container as solution path sterility may be impaired. Some opacity of the plastic due to moisture absorption during the sterilization process may be observed. This is normal and does not affect the solution quality or safety. The opacity will diminish gradually. Check for minute leaks by squeezing inner bag firmly. If leaks are found, discard solution as sterility may be impaired. If supplemental medication is desired, follow directions below.

Preparation for Administration

1. Suspend container from eyelet support.
2. Remove plastic protector from outlet port at bottom of container.
3. Attach administration set. Refer to complete directions accompanying set.

To Add Medication

WARNING: Additives may be incompatible.

To add medication before solution administration

1. Prepare medication site.
2. Using syringe with 19 to 22 gauge needle, puncture medication port and inject.
3. Mix solution and medication thoroughly. For high density medication such as potassium chloride, squeeze ports while ports are upright and mix thoroughly.

To add medication during solution administration
1. Close clamp on the set.
2. Prepare medication site.
3. Using syringe with 19 to 22 gauge needle, puncture resealable
medication port and inject.
4. Remove container from IV pole and/or turn to an upright position.
5. Evacuate both ports by squeezing them while container is in the upright position.
6. Mix solution and medication thoroughly.
7. Return container to in use position and continue administration.

CAUTION: Federal (USA) law restricts this drug to use by or on the order of a licensed veterinarian.

Baxter Healthcare Corporation
Deerfield, IL 60015 USA
For customer service call (800) 933-0303
Printed in USA

Baxter is a registered trademark of Baxter International, Inc.

07-19-00-0639
Rev. January 2019

Container Label

Veterinary Lactated
Ringer’s Injection USP

5000 mL

EACH 100 ML CONTAINS 600 MG SODIUM CHLORIDE USP
310 MG SODIUM LACTATE 30 MG POTASSIUM CHLORIDE USP
20 MG CALCIUM CHLORIDE USP PH 6.5 (6.0 TO 7.5) MEQ/L
SODIUM 130 POTASSIUM 4 CALCIUM 2.7 CHLORIDE 109
LACTATE 28 OSMOLARITY 273 MOSMOL/L (CALC)
STERILE NONPYROGENIC SINGLE DOSE CONTAINER CONTAINS
NO ANTIMICROBIALAGENTS USE SOLUTION PROMPTLY
FOLLOWING INITIALENTRY NOT FOR USE INTHE TREATMENT
OF LACTIC ACIDOSIS ADDITIVES MAY BE INCOMPATIBLE
CONSULT WITH PHARMACIST IF AVAILABLE WHEN INTRODUCING
ADDITIVES USE ASEPTIC TECHNIQUE MIX THOROUGHLY DISCARD
UNUSED PORTION DOSAGE INTRAVENOUSLY AS DIRECTED BY
A VETERINARIAN SEE PACKAGE INSERT CAUTIONS SQUEEZE
AND INSPECT INNER BAG WHICH MAINTAINS PRODUCT
STERILITY DISCARD IF LEAKS ARE FOUND DO NOT ADMINISTER
SIMULTANEOUSLY WITH BLOOD DO NOT USE UNLESS SOLUTION
IS CLEAR AND SEALIS INTACT STORE UNIT IN MOISTURE
BARRIER OVERWRAP AT ROOM TEMPERATURE (25°C/77°F)
UNTIL READY TO USE AVOID EXCESSIVE HEAT

FOR ANIMAL USE ONLY
CAUTION FEDERAL(USA) LAW RESTRICTS THIS DRUG TO USE BY
OR ON THE ORDER OF A LICENSED VETERINARIAN
BAXTER IS A REGISTERED TRADEMARK OF BAXTER INTERNATIONAL, INC.

FOR CUSTOMER SERVICE CALL
800 933 0303

BAXTER HEALTHCARE CORPORATION
DEERFIELD, IL 60015 USA

MADE IN USA

NDC 0338-0092-02
2B8219
07-25-00-0419

Baxter Logo

4500

4000

3500

3000

2500

2000

1500

1000

500